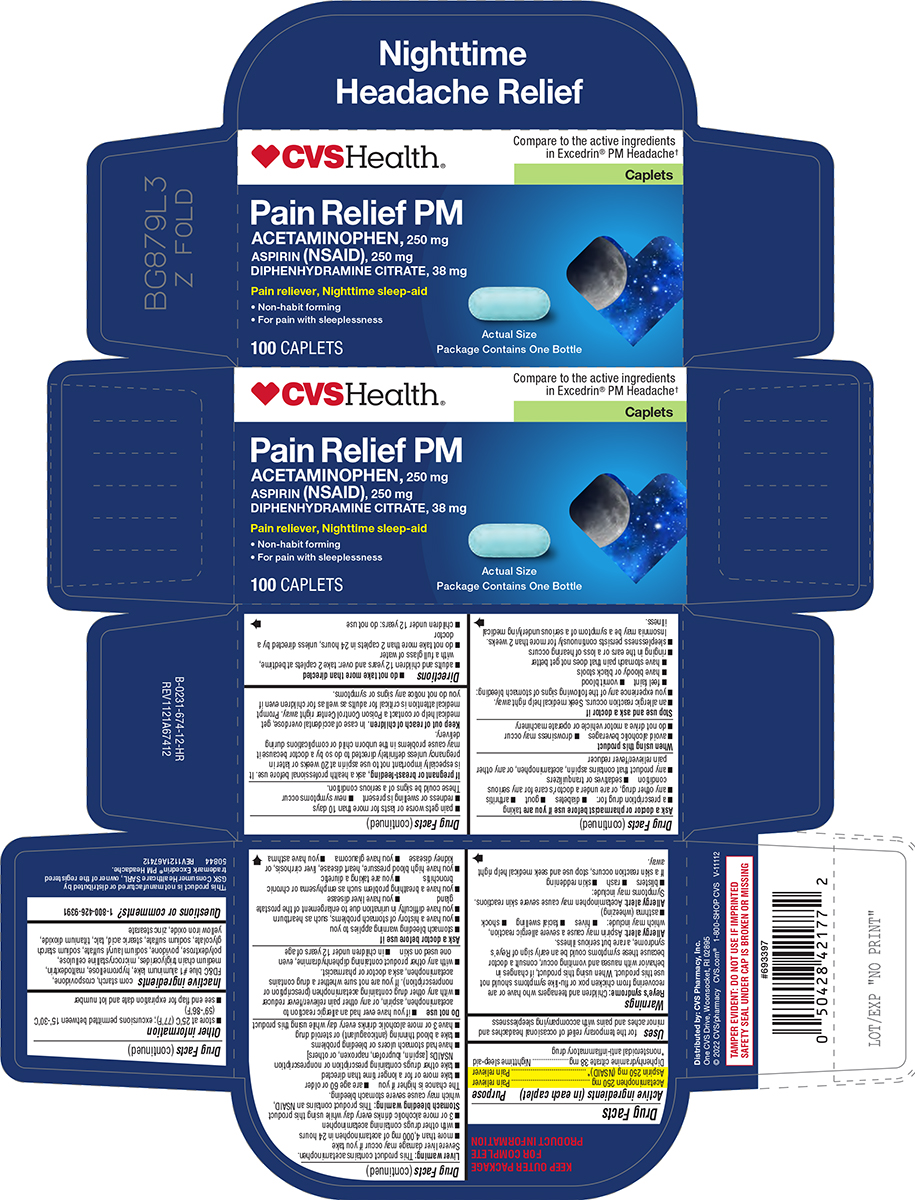 DRUG LABEL: Pain Relief PM
NDC: 59779-894 | Form: TABLET, FILM COATED
Manufacturer: CVS Pharmacy
Category: otc | Type: HUMAN OTC DRUG LABEL
Date: 20260211

ACTIVE INGREDIENTS: ACETAMINOPHEN 250 mg/1 1; ASPIRIN 250 mg/1 1; DIPHENHYDRAMINE CITRATE 38 mg/1 1
INACTIVE INGREDIENTS: STARCH, CORN; CROSPOVIDONE, UNSPECIFIED; FD&C BLUE NO. 1 ALUMINUM LAKE; HYPROMELLOSE, UNSPECIFIED; MALTODEXTRIN; MEDIUM-CHAIN TRIGLYCERIDES; MICROCRYSTALLINE CELLULOSE; POLYDEXTROSE; POVIDONE, UNSPECIFIED; SODIUM LAURYL SULFATE; SODIUM STARCH GLYCOLATE TYPE A POTATO; SODIUM SULFATE; STEARIC ACID; TALC; TITANIUM DIOXIDE; FERRIC OXIDE YELLOW; ZINC STEARATE

CVS 44-674-Delisted

Active ingredients (in each caplet)

Acetaminophen 250 mg
Aspirin 250 mg (NSAID)*
Diphenhydramine citrate 38 mg
*nonsteroidal anti-inflammatory drug

Purpose

Pain reliever
Pain reliever
Nighttime sleep-aid

Uses

for the temporary relief of occasional headaches and minor aches and pains with accompanying sleeplessness

Warnings

Reye's syndrome: Children and teenagers who have or are recovering from chicken pox or flu-like symptoms should not use this product. When using this product, if changes in behavior with nausea and vomiting occur, consult a doctor because these symptoms could be an early sign of Reye's syndrome, a rare but serious illness.

Allergy alert: Aspirin may cause a severe allergic reaction, which may include:

- hives
- facial swelling
- shock
- asthma (wheezing)

Allergy alert: Acetaminophen may cause severe skin reactions. Symptoms may include:

- blisters
- rash
- skin reddening

If a skin reaction occurs, stop use and seek medical help right away.

Liver warning: This product contains acetaminophen. Severe liver damage may occur if you take

- more than 4,000 mg of acetaminophen in 24 hours
- with other drugs containing acetaminophen
- 3 or more alcoholic drinks every day while using this product

Stomach bleeding warning: This product contains an NSAID, which may cause severe stomach bleeding. The chance is higher if you

- are age 60 or older
- take more or for a longer time than directed
- take other drugs containing prescription or nonprescription NSAIDs [aspirin, ibuprofen, naproxen, or others]
- have had stomach ulcers or bleeding problems
- take a blood thinning (anticoagulant) or steroid drug
- have 3 or more alcoholic drinks every day while using this product

Do not use

- if you have ever had an allergic reaction to acetaminophen, aspirin, or any other pain reliever/fever reducer
- with any other drug containing acetaminophen (prescription or nonprescription). If you are not sure whether a drug contains acetaminophen, ask a doctor or pharmacist.
- with any other product containing diphenhydramine, even one used on skin
- in children under 12 years of age

Ask a doctor before use if

- stomach bleeding warning applies to you
- you have a history of stomach problems, such as heartburn
- you have difficulty in urination due to enlargement of the prostate gland
- you have liver disease
- you have a breathing problem such as emphysema or chronic bronchitis
- you are taking a diuretic
- you have high blood pressure, heart disease, liver cirrhosis, or kidney disease
- you have glaucoma
- you have asthma

Ask a doctor or pharmacist before use if you are taking

- a prescription drug for:
  - diabetes
  - gout
  - arthritis
- any other drug, or are under a doctor’s care for any serious condition
- sedatives or tranquilizers
- any product that contains aspirin, acetaminophen, or any other pain reliever/fever reducer

When using this product

- avoid alcoholic beverages
- drowsiness may occur
- do not drive a motor vehicle or operate machinery

Stop use and ask a doctor if

- an allergic reaction occurs. Seek medical help right away.
- you experience any of the following signs of stomach bleeding:
  - feel faint
  - vomit blood
  - have bloody or black stools
  - have stomach pain that does not get better
- ringing in the ears or a loss of hearing occurs
- sleeplessness persists continuously for more than 2 weeks. Insomnia may be a symptom of a serious underlying medical illness.
- pain gets worse or lasts for more than 10 days
- redness or swelling is present
- new symptoms occur

These could be signs of a serious condition.

If pregnant or breast-feeding,

ask a health professional before use. It is especially important not to use aspirin at 20 weeks or later in pregnancy unless definitely directed to do so by a doctor because it may cause problems in the unborn child or complications during delivery.

Keep out of reach of children.

In case of accidental overdose, get medical help or contact a Poison Control Center right away. Prompt medical attention is critical for adults as well as for children even if you do not notice any signs or symptoms.

Directions

- do not take more than directed
- adults and children 12 years and over: take 2 caplets at bedtime, with a full glass of water
- do not take more than 2 caplets in 24 hours, unless directed by a doctor
- children under 12 years: do not use

Other information

- store at 25°C (77°F); excursions permitted between 15°-30°C (59°-86°F)
- see end flap for expiration date and lot number

Inactive ingredients

corn starch, crospovidone, FD&C blue #1 aluminum lake, hypromellose, maltodextrin, medium chain triglycerides, microcrystalline cellulose, polydextrose, povidone, sodium lauryl sulfate, sodium starch glycolate, sodium sulfate, stearic acid, talc, titanium dioxide, yellow iron oxide, zinc stearate

Questions or comments?

1-800-426-9391

Principal Display Panel

♥︎CVSHealth®

Compare to the active ingredients
in Excedrin® PM Headache†

Caplets

Pain Relief PM
ACETAMINOPHEN, 250 mg
ASPIRIN (NSAID), 250 mg
DIPHENHYDRAMINE CITRATE, 38 mg

Pain reliever, Nighttime sleep-aid

• Non-habit forming
• For pain with sleeplessness

100 CAPLETS

Actual Size

Package Contains One Bottle

TAMPER EVIDENT: DO NOT USE IF IMPRINTED
SAFETY SEAL UNDER CAP IS BROKEN OR MISSING

†This product is not manufactured or distributed by
GSK Consumer Healthcare SARL, owner of the registered
trademark Excedrin® PM Headache.
50844 REV1121A67412

Distributed by: CVS Pharmacy, Inc.
One CVS Drive, Woonsocket, RI 02895
© 2022 CVS/pharmacy CVS.com® 1-800-SHOP CVS V-11112

CVS 44-674